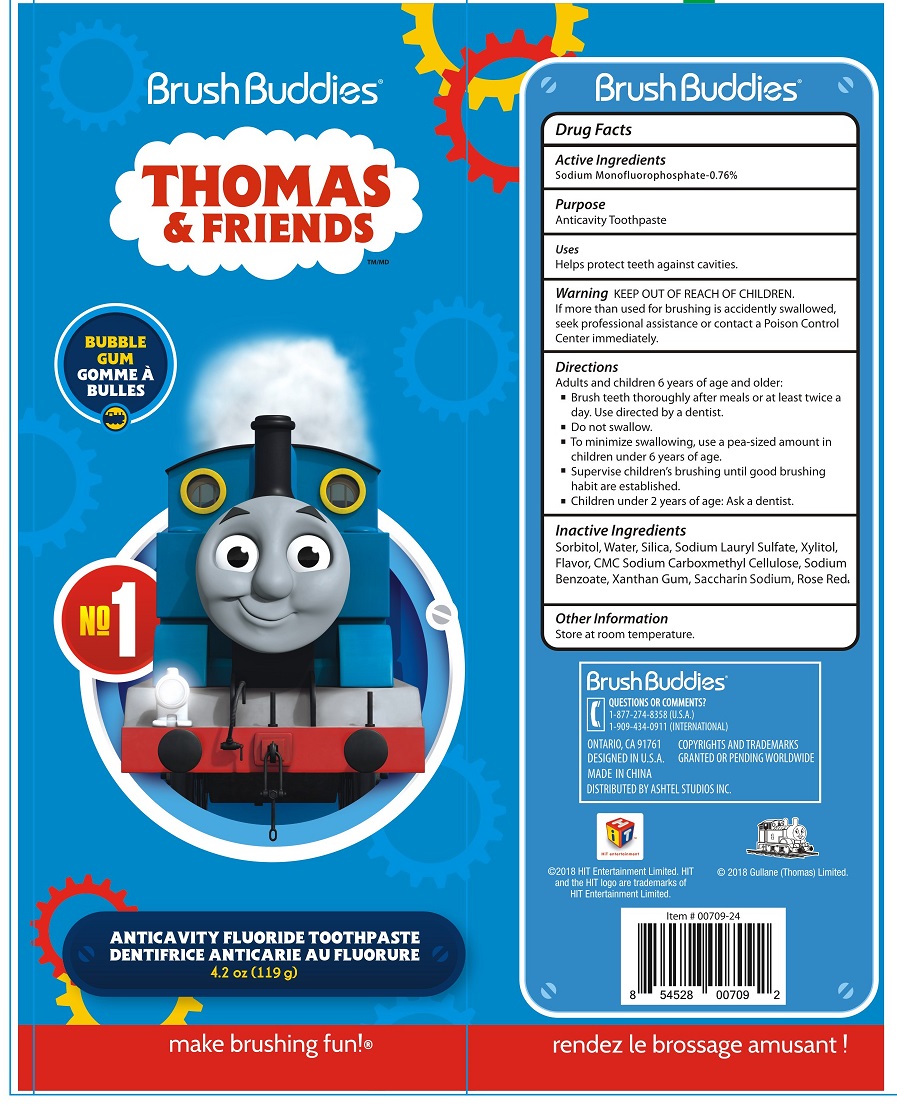 DRUG LABEL: Thomas and Friends
NDC: 70108-017 | Form: PASTE, DENTIFRICE
Manufacturer: Ashtel Studios, Inc.
Category: otc | Type: HUMAN OTC DRUG LABEL
Date: 20180817

ACTIVE INGREDIENTS: SODIUM MONOFLUOROPHOSPHATE 0.76 g/100 g
INACTIVE INGREDIENTS: SORBITOL; WATER; SILICON DIOXIDE; SODIUM LAURYL SULFATE; XYLITOL; CARBOXYMETHYLCELLULOSE SODIUM, UNSPECIFIED FORM; SODIUM BENZOATE; XANTHAN GUM; SACCHARIN SODIUM; ROSE BENGAL SODIUM

Thomas & Friends Toothpaste

Active Ingredients

Sodium Monofluorophosphate-0.76%

Purpose

Anticavity Toothpaste

Uses

Helps protect teeth against cavities.

Warning

If more than used for brushing is accidently swallowed, seek professional assistance or contact a Poison Control Center immediately.

KEEP OUT OF REACH OF CHILDREN.

Directions

Adults and children 6 years of age and older:

- Brush teeth thoroughly after meals or at least twice a day. Use as directed by a dentist.
- Do not swallow.
- To minimize swallowing, use a pea-sized amount in children under 6 years of age.
- Supervise children's brushing until good brushing habit are established.
- Children under 2 years of age: Ask a dentist.

Inactive Ingredients

Sorbitol, Water, Silica, Sodium Lauryl Sulfate, Xylitol, Flavor, CMC Sodium Carboxymethyl Cellulose, Sodium Benzoate, Xanthan Gum, Saccharin Sodium, Rose Red

Other Information

Store at room temperature.

BUBBLE GUM

ANTICAVITY FLUORIDE TOOTHPASTE

Make brushing fun!®

QUESTIONS OR COMMENTS?

1-877-274-8358 (U.S.A.)

1-909-434-0911 (INTERNATIONAL)

ONTARIO, CA 91761

DESIGNED IN U.S.A.

MADE IN CHINA

DISTRIBUTED BY ASHTEL STUDIOS INC.